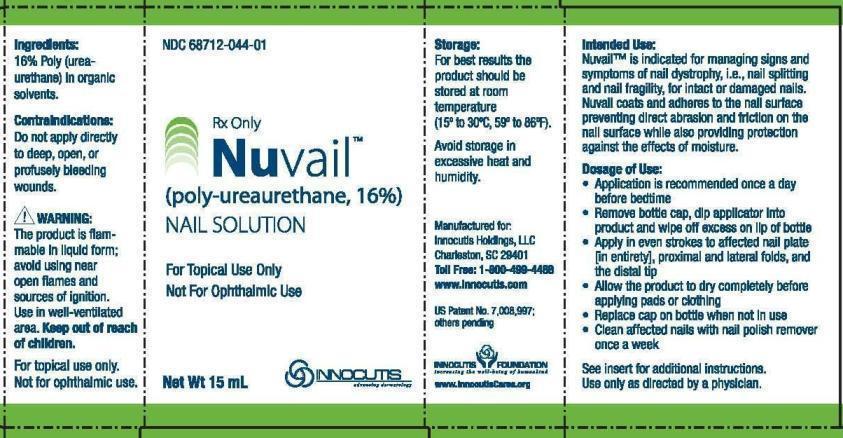 DRUG LABEL: Nuvail
NDC: 52512-710
Manufacturer: Ei Inc.
Category: other | Type: PRESCRIPTION MEDICAL DEVICE LABEL
Date: 20130418
INACTIVE INGREDIENTS: ACETONE; METHYL ETHYL KETONE; ETHYLENE GLYCOL; PROPYLENE GLYCOL; 1,2-ETHANEDITHIOL

Nuvail

Intended Use

Nuvail™ is indicated for managing signs and symptoms of nail dystrophy, i.e., nail splitting and nail fragility, for intact or damaged nails.
Nuvail coats and adheres to the nail surface preventing direct abrasion and friction on the nail surface while also providing protection
against the effects of moisture.

Product Description

The product is a biocompatible, polymeric solution which forms a uniform film when applied to the nail. The product is dispersed in a noncytotoxic solution which dries rapidly, adhering to the contours of the nail to form a flexible, waterproof barrier. The film will wear off naturally and must be re-applied as directed to be effective. The film is colorless, transparent and possesses good moisture vapor permeability.

Ingredients

16% Poly (urea-urethane) in organic solvents

Contraindications

Do not apply directly to deep, open, or profusely bleeding wounds.

Warnings and Precautions

The product is flammable in liquid form; avoid using near open flames and sources of ignition. Use in well-ventilated area. Keep out of reach
of children.

Store at room temperature away from heat. Do not allow product to come into contact with floors, counter tops, furniture or other finished
surfaces - will stain.

May temporarily sting upon application. Persons sensitized to isocyanate should not use this product. Should redness or other signs of
irritation appear, discontinue use and consult your healthcare provider.

Use of other products, ointments, creams or lotions before application of this product may prevent the film from forming correctly and
reduce effectiveness.

Directions for use

Application is recommended once a daybefore bedtime

Remove bottle cap, dip applicator into product and wipe off excess on lip of bottle

Apply in even strokes to affected nail plate[in entirety], proximal and lateral folds, and the distal tip

Allow the product to dry completely before applying pads or clothing

Replace cap on bottle when not in use

Clean affected nails with nail polish remover once a week

How Supplied

Nuvail Nail Solution is suppled in a: 15 ML non-sterile bottle with applicator 68712-044-01
Manufactured for: Inncoutis Holdings LLC, Charleston SC 29401
1-800-499-4468 www.Innocutis.com

Storage

For best results the product should be stored at room temperature (15º to 30ºC, 59º to 86ºF). Avoid storage in excessive heat and humidity.
Refer to the bottle label for expiration date.